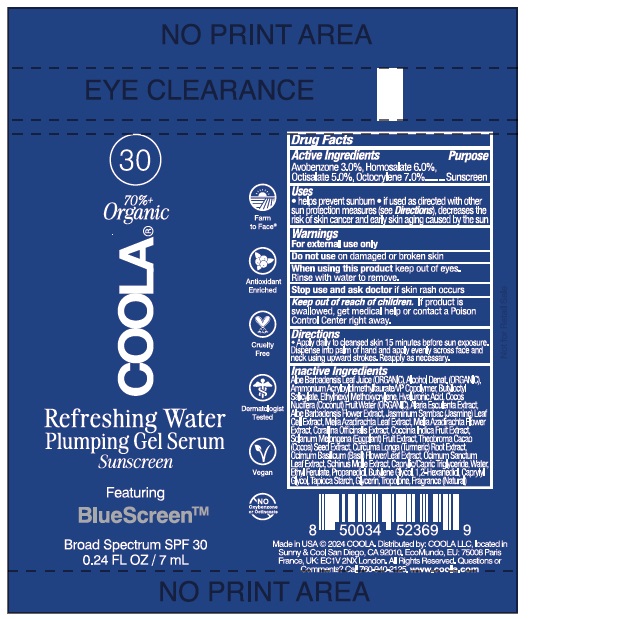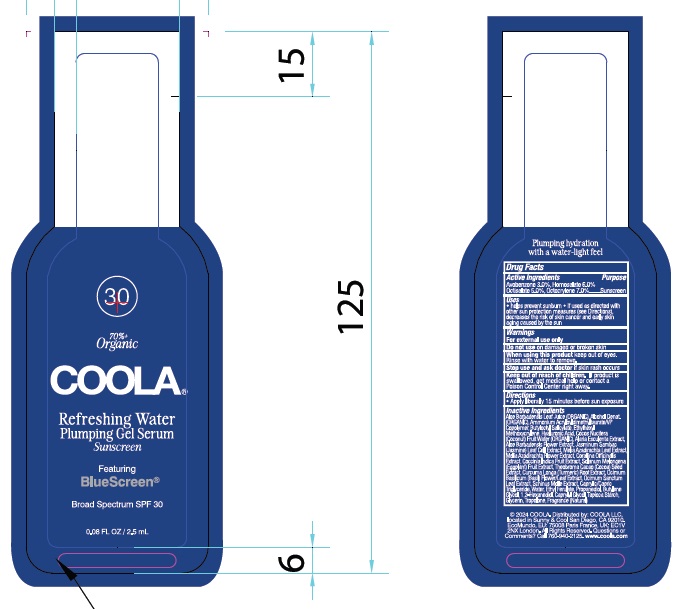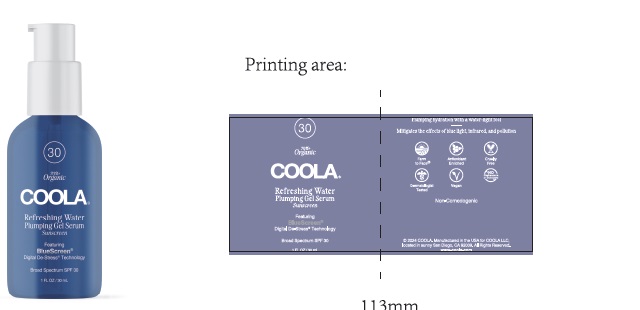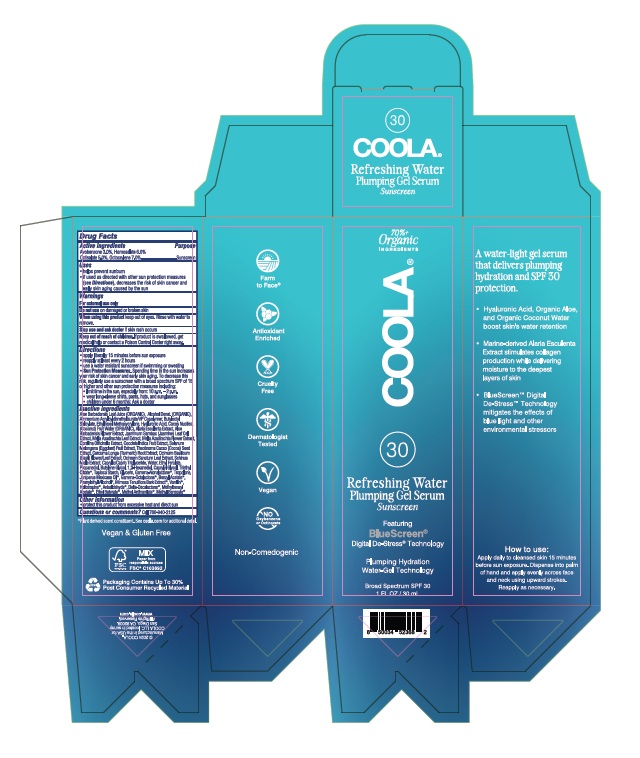 DRUG LABEL: COOLA Refreshing Water Plumping Gel Serum SPF 30
NDC: 79753-081 | Form: GEL
Manufacturer: COOLA LLC
Category: otc | Type: HUMAN OTC DRUG LABEL
Date: 20231129

ACTIVE INGREDIENTS: AVOBENZONE 3.0 g/100 mL; HOMOSALATE 6.0 g/100 mL; OCTISALATE 5.0 g/100 mL; OCTOCRYLENE 7.0 g/100 mL
INACTIVE INGREDIENTS: ALOE VERA LEAF; ALCOHOL; AMMONIUM ACRYLOYLDIMETHYLTAURATE/VP COPOLYMER; BUTYLOCTYL SALICYLATE; ETHYLHEXYL METHOXYCRYLENE; HYALURONIC ACID; COCONUT WATER; ALARIA ESCULENTA; ALOE VERA FLOWER; JASMINUM OFFICINALE LEAF; AZADIRACHTA INDICA LEAF; AZADIRACHTA INDICA FLOWER; CORALLINA OFFICINALIS; COCCINIA GRANDIS FRUIT; EGGPLANT; COCOA; TURMERIC; HOLY BASIL LEAF; OCIMUM BASILICUM FLOWERING TOP; SCHINUS MOLLE FRUITING TOP; MEDIUM-CHAIN TRIGLYCERIDES; WATER; ETHYL FERULATE; PROPANEDIOL; BUTYLENE GLYCOL; 1,2-HEXANEDIOL; CAPRYLYL GLYCOL; TRIETHYL CITRATE; STARCH, TAPIOCA; GLYCERIN; .GAMMA.-NONALACTONE; TROPOLONE; JUNIPERUS DEPPEANA WOOD OIL; .GAMMA.-OCTALACTONE; BENZYL ACETATE; PHENYLETHYL ALCOHOL; MIMOSA TENUIFLORA BARK; VANILLIN; PIPERONAL; P-ANISALDEHYDE; .DELTA.-DECALACTONE; METHYLBENZYL ACETATE; ETHYL BUTYRATE; METHYL ANTHRANILATE; METHYL BENZOATE

COOLA Refreshing Water Plumping Gel Serum SPF 30

Drug Facts

Active Ingredients

Avobenzone 3.0%, Homosalate 6.0%, Octisalate 5.0%, Octocrylene 7.0%

Purpose

Suncreen

Uses

- helps prevent sunburn

- if used as directed with other sun protection measures

(see Directions), decreases the risk of skin cancer and

early skin aging caused by the sun

Warnings

For external use only

Do not use on damaged or broken skin

When using this product keep out of eyes. Rinse with water to remove.

Stop use and ask doctor if skin rash occurs

Keep out of reach of children. If product is swallowed, get

medical help or contact a Poison Control Center right away.

Directions
● apply liberally 15 minutes before sun exposure.
● reapply at least every 2 hours
● use a water resistant sunscreen if wimming or sweating
Sun Protection Measures. Spending time in the sun
increases your risk of skin cancer and early skin aging. To
decrease this risk, regularly use a sunscreen with a broad
spection SPF of 15 or higher and other sun protection
measures including:
● limit time in the sun, especially from: 10 a.m. - 2 p.m.
● wear long-sleeve shirts, pants, hats, and sunglasses
●children under 6 months: Ask a doctor

Inactive Ingredients
Aloe Barbadensis Leaf Juice (ORGANIC), Alcohol Denat (ORGANIC),
Ammonium Acryloyldimethyltaurate/VP Copolymer Butyloctyl
Salicylate, Ethylhexyl Methoxycrylene, Hyaluronic Acid, Cocos Nucifera
(Coconut) Fruit Water (ORGANIC), Alaria Esculenta Extract, Aloe
Barbadensis Flower Extract, Jasminum Sambac (Jasmine) Leaf Cell
Extract, Melia Azadirachta Leaf Extract, Melia Azadirachta Flower Extract,
Corallina Officinalis Extract, Coccinia Indica Fruit Extract, Solanum
Melongena (Eggplant) Fruit Extract, Theobroma Cacao (Cocoa) Seed
Extract, Curcuma Longa (Turmeric) Root Extract, Ocimum Basilicum
(Basil) Flower/Leaf Extract, Ocimum Sanctum Leaf Extract, Schinus
Molle Extract, Caprylic/Capric Triglyceride, Water, Ethyl Ferulate,
Propanediol, Butylene Glycol, 1,2-Hexanediol, Caprylyl Glycol, Triethyl
Citrate*, Tapioca Starch, Glycerin, Gamma-Nonalactone*, Tropolone,
Juniperus Mexicana Oil*, Gamma-Octalactone*, Benzyl Acetate*,
Phenylethyl Alcohol*, Mimosa Tenuiflora Bark Extract*, Vanillin*,
Heliotropine*, Anisaldehyde*, Delta-Decalactone*, Methylbenzyl
Acetate*, Ethyl Butyrate*, Methyl Anthranilate*, Methyl Benzoate*

*Plant derived scent constituent. See coola.com for additional detail.

Other information

- protect this product from excessive heat and direct sun

Questions or comments? Call 760-940-2125

COOLA Refreshing Water Plumping Gel Serum - Labeling

COOLA®
Refreshing Water
Plumping Gel Serum
Sunscreen

Broad Spectrum SPF 30

©2024 COOLA
Manufactured in the USA for
COOLA LLC, located in sunny
San Diego, CA 92009.
All Rights Reserved.
www.coola.com

Carton

Bottle

Tube

Sachet

res